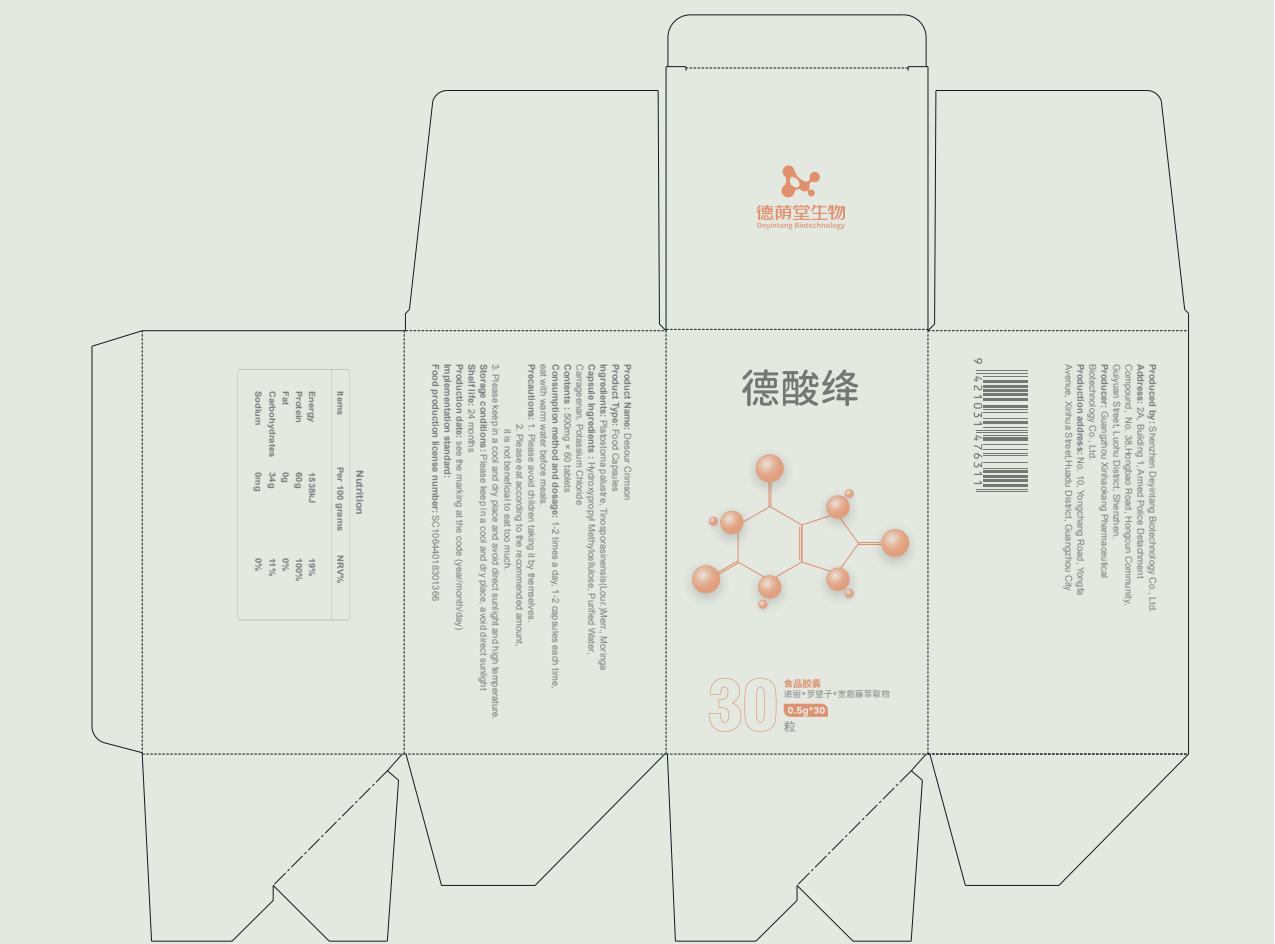 DRUG LABEL: Desour Crimson
NDC: 82570-013 | Form: CAPSULE
Manufacturer: Shenzhen Deyintang Biotechnology Co., Ltd.
Category: otc | Type: HUMAN OTC DRUG LABEL
Date: 20220221

ACTIVE INGREDIENTS: TINOSPORA SINENSIS STEM 22 g/100 g; PLATOSTOMA PALUSTRE WHOLE 20 g/100 g; MORINGA OLEIFERA LEAF 20 g/100 g; MORINDA CITRIFOLIA FRUIT 20 g/100 g
INACTIVE INGREDIENTS: POTASSIUM CHLORIDE; CARRAGEENAN; HYPROMELLOSES

ACTIVE INGREDIENT

Platostoma palustre,Tinosporasinensis(Lour.)Merr.,Moringa

INACTIVE INGREDIENT

Hydroxypropyl Methylcellulose,Purified Water,Carrageenan,Potassium Chloride

PURPOSE

health care

Please avoid children taking it by themselves.

Consumption method and dosage

1-2 times a day, 1-2 capsules each time,eat with warm water before meals.

INDICATIONS AND USAGE

Please eat according to the recommended amount,it is not beneficial to eat too much.

Storage conditions

Please keep in a cool and dry place, avoid direct sunlight

WARNINGS

1.Please avoid children taking it by themselves.
2.Please eat according to the recommended amount,it is not beneficial to eat too much.
3.Please keep in a cool and dry place and avoid direct sunlight and high temperature.